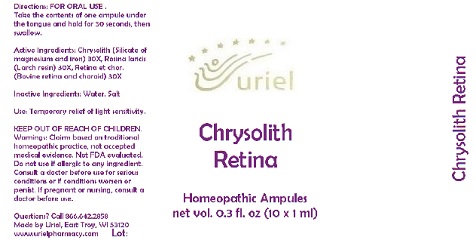 DRUG LABEL: Chrysolith Retina
NDC: 48951-3086 | Form: LIQUID
Manufacturer: Uriel Pharmacy Inc.
Category: homeopathic | Type: HUMAN OTC DRUG LABEL
Date: 20180516

ACTIVE INGREDIENTS: SILICON DIOXIDE 30 [hp_X]/1 mL; LARIX DECIDUA RESIN 30 [hp_X]/1 mL; BOS TAURUS EYE 30 [hp_X]/1 mL
INACTIVE INGREDIENTS: WATER; SODIUM CHLORIDE

Chrysolith Retina

INDICATIONS AND USAGE

Directions: FOR ORAL USE .

DOSAGE AND ADMINISTRATION

Take the contents of one ampule under the tongue and hold for 30 seconds, then swallow.

ACTIVE INGREDIENT

Active Ingredients: Chrysolith (Silicate of magnesium and iron) 30X, Resina laricis (Larch resin) 30X, Retina et chor. (Bovine retina and choroid) 30

Inactive Ingredients: Water, Salt

PURPOSE

Use: Temporary relief of light sensitivity.

KEEP OUT OF REACH OF CHILDREN.

WARNINGS

Warnings: Claims based on traditional homeopathic practice, not accepted medical evidence. Not FDA evaluated. Do not use if allergic to any ingredient. Consult a doctor before use for serious conditions or if conditions worsen or persist. If pregnant or nursing, consult a doctor before use.

QUESTIONS

Questions? Call 866.642.2858 Made by Uriel, East Troy, WI 53120 www.urielpharmacy.com